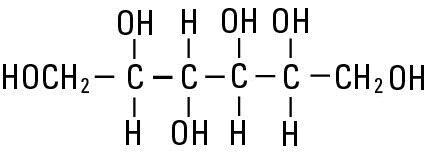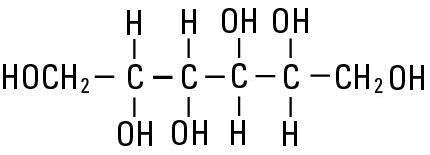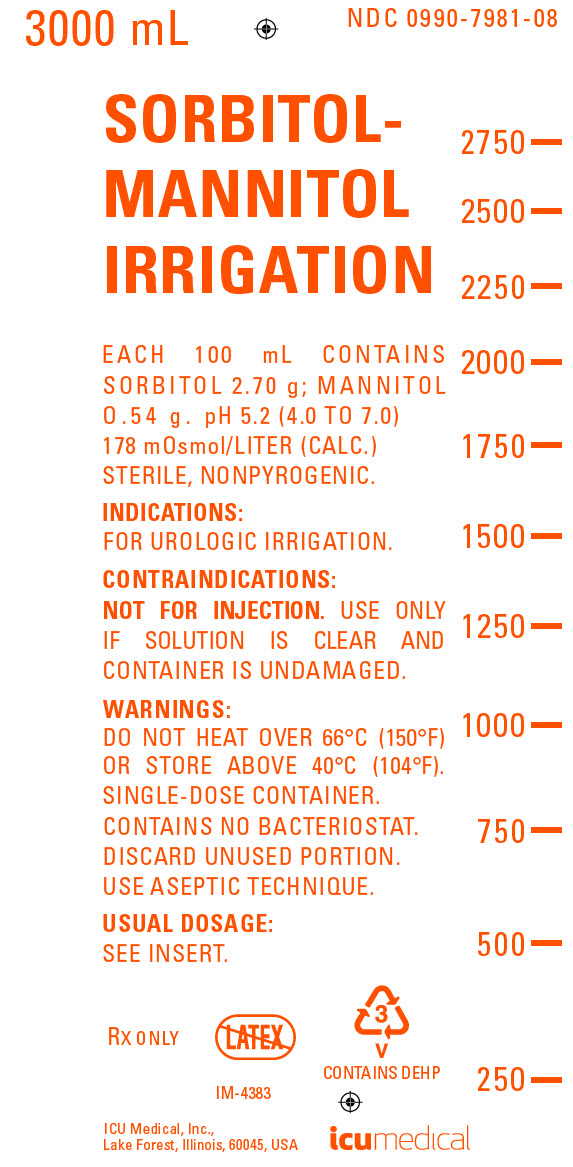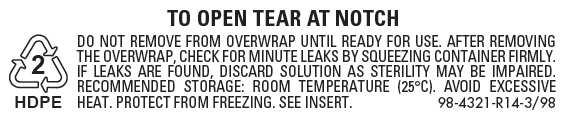 DRUG LABEL: Sorbitol-Mannitol
NDC: 0990-7981 | Form: IRRIGANT
Manufacturer: ICU Medical Inc.
Category: prescription | Type: HUMAN PRESCRIPTION DRUG LABEL
Date: 20251030

ACTIVE INGREDIENTS: SORBITOL 2.7 g/100 mL; MANNITOL 0.54 g/100 mL
INACTIVE INGREDIENTS: WATER

SORBITOL-MANNITOL IRRIGATION

NONELECTROLYTIC IRRIGATING FLUID FOR TRANSURETHRAL SURGICAL PROCEDURES
For Urologic Irrigation Only; Not For Injection By Usual Parenteral Routes.
Flexible Irrigation Container

Rx only

DESCRIPTION

Sorbitol-Mannitol Irrigation is a sterile, nonpyrogenic, hypotonic, aqueous solution for urologic nonelectrolyte irrigation during transurethral surgical procedures. Each 100 mL contains sorbitol 2.70 g and mannitol 0.54 g in water for injection. The solution is nonelectrolytic and hypotonic (178 mOsmol/liter calc.); pH 5.2 (4.0 to 7.0).

The solution contains no bacteriostat, antimicrobial agent or added buffer and is intended only for use as a single-dose irrigation. When smaller volumes are required the unused portion should be discarded.

Sorbitol-Mannitol Irrigation is a nonelectrolyte urologic irrigant.

Sorbitol, NF is chemically designated D-glucitol (C6H14O6), white powder, granules or flakes very soluble in water. It has the following structural formula:

Mannitol, USP is chemically designated D-mannitol (C6H14O6), white crystalline powder or free-flowing granules, freely soluble in water. It has the following structural formula:

Water for Injection, USP is chemically designated H20.

The flexible plastic container is fabricated from a specially formulated polyvinylchloride. Water can permeate from inside the container into the overwrap but not in amounts sufficient to affect the solution significantly.

The semi-rigid container is fabricated from a specially formulated polyolefin. It is a copolymer of ethylene and propylene. The container requires no vapor barrier to maintain the proper drug concentration.

Solutions in contact with the plastic container may leach out certain chemical components from the plastic in very small amounts; however, biological testing was supportive of the safety of the plastic container materials.

Exposure to temperatures above 25°C/77°F during transport and storage will lead to minor losses in moisture content. Higher temperatures lead to greater losses. It is unlikely that these minor losses will lead to clinically significant changes within the expiration period.

CLINICAL PHARMACOLOGY

Sorbitol and mannitol are hexitols and are nonelectrolytes. A solution of these constituents in water is therefore nonconductive and suitable for urologic irrigation during electrosurgical procedures. A 3% (approx.) total concentration of sorbitol-mannitol contains sufficient solute to minimize the risk of intravascular hemolysis which can occur from absorption of plain water through open prostatic veins during transurethral resection (TUR). Any solution that is absorbed intravascularly during transurethral prostatic or bladder surgery, although variable in amount depending primarily on the extent of surgery, will be excreted by the kidney. When absorbed intravascularly, sorbitol and mannitol act as osmotic diuretics.

Intravascular absorption of sorbitol has been shown to produce elevations of serum lactate after TUR above preoperative values owing to sorbitol's favored metabolism to lactate from pyruvate. Increased lactate levels were not sufficient to produce evidence of metabolic acidosis. Mannitol is only slightly metabolized and rapidly excreted by the kidney.

INDICATIONS AND USAGE

Sorbitol-Mannitol Irrigation is indicated for use as a urologic irrigating fluid during transurethral prostatic resection and other transurethral surgical procedures.

CONTRAINDICATIONS

NOT FOR INJECTION BY USUAL PARENTERAL ROUTES.

Do not use in patients with anuria.

WARNINGS

FOR UROLOGIC IRRIGATION ONLY.

Solutions for urologic irrigation must be used with caution in patients with severe cardiopulmonary or renal dysfunction.

Irrigating fluids used during transurethral prostatectomy have been demonstrated to enter the systemic circulation in relatively large volumes; thus, sorbitol-mannitol irrigant must be regarded as a systemic drug. Absorption of large amounts of fluids containing sorbitol-mannitol and the osmotic diuresis it produces may significantly alter cardiopulmonary and renal dynamics.

Hyperglycemia from metabolism of sorbitol may occur in patients with diabetes mellitus.

Hyperlactatemia from metabolism of sorbitol may potentially produce a significant lactic acidemia in metabolically compromised patients.

The contents of an opened container should be used promptly to minimize the possibility of bacterial growth or pyrogen formation.

Discard the unused portion of irrigation solution since it contains no preservatives. Do not heat over 66°C (150°F).

PRECAUTIONS

Cardiovascular status, especially of the patient with cardiac disease, should be carefully observed before and during transurethral resection of the prostate when using Sorbitol-Mannitol Irrigation, because the quantity of fluid absorbed into the systemic circulation by opened prostatic veins may produce significant expansion of the extracellular fluid and lead to fulminating congestive heart failure.

Shift of sodium-free intracellular fluid into the extracellular compartment following systemic absorption of solution may lower serum sodium concentration and aggravate pre-existing hyponatremia.

Excessive loss of water and electrolytes may lead to serious imbalances. With continuous irrigation, loss of water may occur in excess of electrolytes, producing hypernatremia.

Sustained diuresis that results from transurethral irrigation with Sorbitol-Mannitol Irrigation may obscure and intensify inadequate hydration or hypovolemia.

Aseptic technique is essential for the use of sterile solutions for irrigation. The administration set should be attached promptly. Unused portions should be discarded and a fresh container of appropriate size used for the start-up of each cycle or repeat procedure.

Do not administer unless solution is clear, seal is intact and container is undamaged. Discard unused portion.

Carcinogenesis, Mutagenesis, Impairment of Fertility: Studies with Sorbitol-Mannitol Irrigation have not been performed to evaluate carcinogenic potential, mutagenic potential, or effects on fertility.

Nursing Mothers: Caution should be exercised when Sorbitol-Mannitol Irrigation is administered to a nursing woman.

Pregnancy: Teratogenic Effects.

Pregnancy Category C. Animal reproduction studies have not been conducted with Sorbitol-Mannitol Irrigation. It is also not known whether Sorbitol-Mannitol Irrigation can cause fetal harm when administered to a pregnant woman or can affect reproduction capacity. Sorbitol-Mannitol Irrigation should be given to a pregnant woman only if clearly needed.

Pediatric Use: The safety and effectiveness of Sorbitol-Mannitol Irrigation have not been established. Its limited use in pediatric patients has been inadequate to fully define proper dosage and limitations for use.

ADVERSE REACTIONS

Adverse reactions may result from intravascular absorption of sorbitol and mannitol. The literature reports occasional adverse reactions from intravenous sorbitol-mannitol infusions. Consequences of absorption of urologic irrigating solutions include fluid and electrolyte disturbances such as acidosis, electrolyte loss, marked diuresis, urinary retention, edema, dryness of mouth, thirst and dehydration; cardiovascular disorders such as hypotension, tachycardia, angina-like pains; pulmonary disorders such as pulmonary congestion; and other general reactions such as blurred vision, convulsions, nausea, vomiting, diarrhea, rhinitis, chills, vertigo, backache and urticaria. Allergic reactions from sorbitol-mannitol have also been reported.

Should any adverse reaction occur, discontinue the irrigant, evaluate the patient, institute appropriate therapeutic countermeasures and save the remainder of the fluid for examination if deemed necessary.

OVERDOSAGE

In the event of dehydration, fluid or solute overload, discontinue the irrigation, evaluate the patient and institute corrective measures as indicated. (See WARNINGS, PRECAUTIONS and ADVERSE REACTIONS.)

DOSAGE AND ADMINISTRATION

Sorbitol-Mannitol Irrigation should be administered only by transurethral instillation with appropriate urologic instrumentation. A disposable administration set should be used. The total volume of solution used for irrigation is solely at the discretion of the surgeon.

Height of container(s) above the operating table in excess of 60 cm (approx. 2 ft) has been reported to increase intravascular absorption of the irrigating fluid.

Parenteral drug products should be inspected visually for particulate matter and discoloration prior to administration, whenever container and solution permit. (See PRECAUTIONS.)

HOW SUPPLIED

Sorbitol-Mannitol Irrigation is supplied in single-dose 3000 mL flexible irrigation container
(NDC No. 0409-7981-08 / 0990-7981-08).

ICU Medical is transitioning NDC codes from the "0409" to a "0990" labeler code. Both NDC codes are expected to be in the market for a period of time.

Store at 20 to 25ºC (68 to 77ºF). [See USP Controlled Room Temperature.] Protect from freezing.

Revised: July, 2018

EN-4664

ICU Medical, Inc., Lake Forest, Illinois, 60045, USA

PRINCIPAL DISPLAY PANEL - 3000 mL Bag Label

3000 mL
NDC 0990-7981-08

SORBITOL-
MANNITOL
IRRIGATION

EACH 100 mL CONTAINS
SORBITOL 2.70 g; MANNITOL
0.54 g. pH 5.2 (4.0 TO 7.0)
178 mOsmol/LITER (CALC.)
STERILE, NONPYROGENIC.

INDICATIONS:
FOR UROLOGIC IRRIGATION.

CONTRAINDICATIONS:
NOT FOR INJECTION. USE ONLY
IF SOLUTION IS CLEAR AND
CONTAINER IS UNDAMAGED.

WARNINGS:
DO NOT HEAT OVER 66°C (150°F)
OR STORE ABOVE 40°C (104°F).
SINGLE-DOSE CONTAINER.
CONTAINS NO BACTERIOSTAT.
DISCARD UNUSED PORTION.
USE ASEPTIC TECHNIQUE.

USUAL DOSAGE:
SEE INSERT.

RX ONLY

IM-4383

3
V
CONTAINS DEHP

ICU Medical, Inc.,
Lake Forest, Illinois, 60045, USA

icumedical

PRINCIPAL DISPLAY PANEL - Overwrap Label

2
HDPE

TO OPEN TEAR AT NOTCH

DO NOT REMOVE FROM OVERWRAP UNTIL READY FOR USE. AFTER REMOVING
THE OVERWRAP, CHECK FOR MINUTE LEAKS BY SQUEEZING CONTAINER FIRMLY.
IF LEAKS ARE FOUND, DISCARD SOLUTION AS STERILITY MAY BE IMPAIRED.
RECOMMENDED STORAGE: ROOM TEMPERATURE (25°C). AVOID EXCESSIVE
HEAT. PROTECT FROM FREEZING. SEE INSERT.
98-4321-R14-3/98